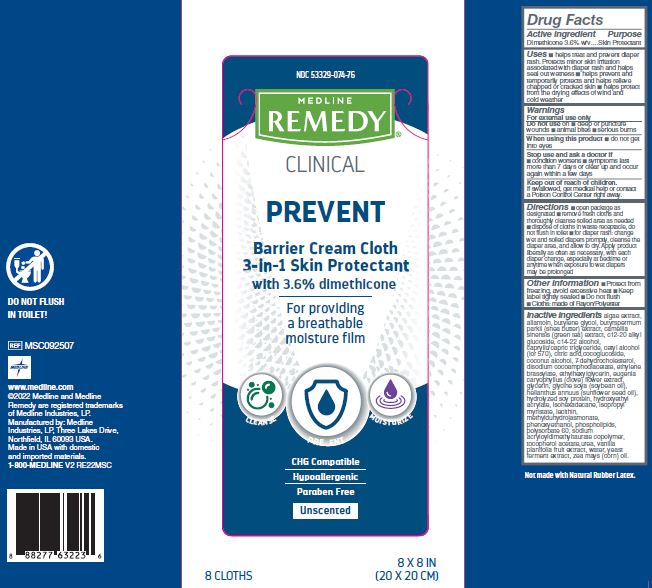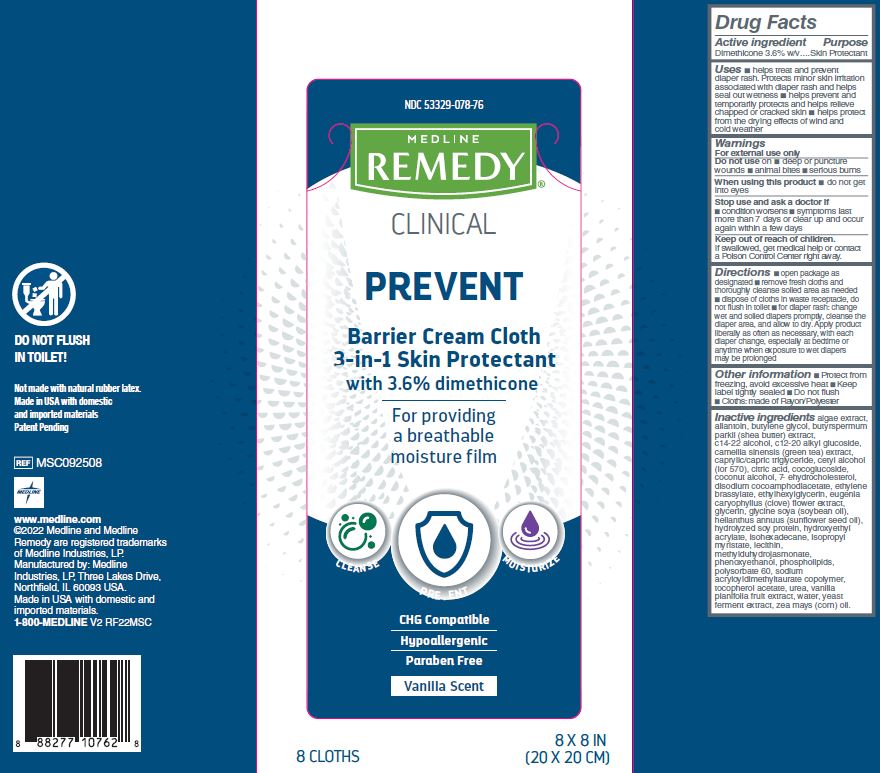 DRUG LABEL: Remedy Barrier Cream Cloths
NDC: 53329-078 | Form: CLOTH
Manufacturer: Medline Industries, LP
Category: otc | Type: HUMAN OTC DRUG LABEL
Date: 20240119

ACTIVE INGREDIENTS: DIMETHICONE 3.6 g/100 mL
INACTIVE INGREDIENTS: HYDROLYZED SOY PROTEIN (ENZYMATIC; 2000 MW); WATER; GLYCERIN; SOYBEAN OIL; CLOVE; SHEA BUTTER; LECITHIN, SOYBEAN; ALLANTOIN; C12-20 ALKYL GLUCOSIDE; C14-22 ALCOHOLS; CETYL ALCOHOL; DISODIUM COCOAMPHODIACETATE; MEDIUM-CHAIN TRIGLYCERIDES; CITRIC ACID MONOHYDRATE; COCO GLUCOSIDE; COCONUT ALCOHOL; ETHYLENE BRASSYLATE; ETHYLHEXYLGLYCERIN; BUTYLENE GLYCOL; ISOPROPYL MYRISTATE; METHYL DIHYDROJASMONATE (SYNTHETIC); YEAST; PHENOXYETHANOL; .ALPHA.-TOCOPHEROL ACETATE; UREA; 7-DEHYDROCHOLESTEROL; SUNFLOWER OIL; CORN OIL; VANILLA; GREEN TEA LEAF; POLYSORBATE 60; ISOHEXADECANE; PHYMATOLITHON CALCAREUM; HYDROXYETHYL ACRYLATE/SODIUM ACRYLOYLDIMETHYL TAURATE COPOLYMER (45000 MPA.S AT 1%)

074 078 Remedy Phytoplex Barrier Cream Cloths

Active ingredient

Dimethicone 3.6% w/w

Purpose

Skin Protectant

Uses

- helps protect from minor skin irritations associated with perineal dermatitis
- temporarily protects and helps relieve chapped or cracked skin
- helps protect from the drying effects of wind and cold weather

Warnings

For external use only

Do not use on

- deep or puncture wounds
- animal bites
- serious burns

When using this product

- do not get into eyes

Stop use and ask a doctor

- condition worsens
- symptoms last more than 7 days or clear up and occur again within a few days

Keep out of reach of children.

If swallowed, get medical help or contact a Poison Control Center right away.

Directions

- Open package as designated
- Remove fresh cloths and thoroughly cleanse soiled area as needed
- Dispose of cloths in waste receptacle, do not flush in toilet
- Single Patient Use only

Other information

- Protect from freezing, avoid excessive heat
- Keep label tightly sealed
- Do Not Flush
- Cloth: made of Rayon/Polyester

Inactive ingredients

algae extract, allantoin, butylene glycol,
butyrospermum parkii (shea butter) extract,
C12-20 alkyl glucoside, C14-22 alcohols,
camellia sinensis (green tea) extract,
caprylic/capric triglyceride, cetyl alcohol,
citric acid, cocoglucoside, coconut alcohol,
7- dehydrocholesterol, disodium
cocoamphodiacetate, ethylene brassylate,
ethylhexylglycerin, eugenia caryophyllus
(clove) flower extract, glycerin, glycine soja
(soybean) oil, helianthus annuus
(sunflower) seed oil, hydrolyzed soy
protein, hydroxyethyl acrylate/sodium
acryloyldimethyltaurate copolymer,
isohexadecane, isopropyl myristate,
lecithin, methyldihydrojasmonate,
phenoxyethanol, phospholipids,
polysorbate 60, tocopheryl acetate, urea,
vanilla plantifolia fruit extract, water, yeast
ferment extract, zea mays (corn) oil.

Manufacturing Information

Manufactured for:

Medline Industries, LP

Three Lakes Drive, Northfield, IL 60093 USA

Made in USA with domestic and imported materials

www.medline.com

1-800-MEDLINE (633-5463)

REF: MSC092508, MSC092507

V2 RE22MSC, V2 RF22MSC